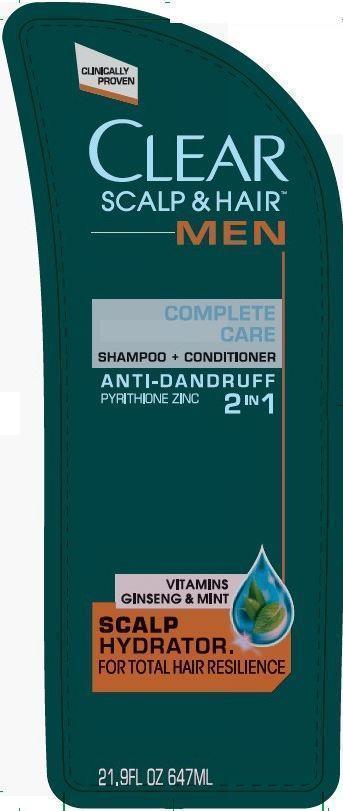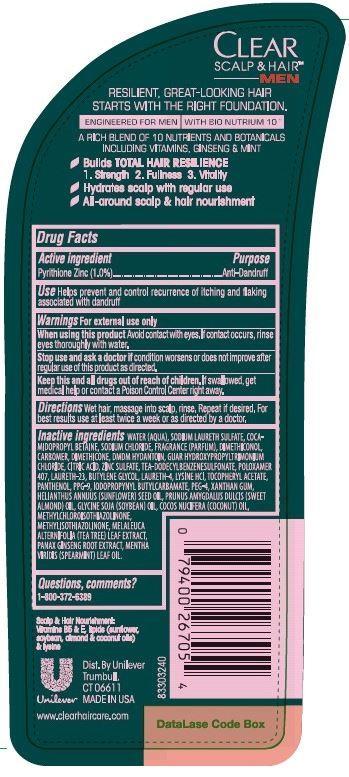 DRUG LABEL: Clear
NDC: 64942-1269 | Form: SHAMPOO
Manufacturer: Conopco Inc. d/b/a Unilever
Category: otc | Type: HUMAN OTC DRUG LABEL
Date: 20150923

ACTIVE INGREDIENTS: Pyrithione Zinc 1 g/100 mL
INACTIVE INGREDIENTS: WATER; SODIUM LAURETH SULFATE; COCAMIDOPROPYL BETAINE; SODIUM CHLORIDE; XANTHAN GUM; DMDM HYDANTOIN; TRIETHANOLAMINE DODECYLBENZENESULFONATE; SUNFLOWER OIL; CITRIC ACID MONOHYDRATE; PPG-9; METHYLCHLOROISOTHIAZOLINONE; METHYLISOTHIAZOLINONE; SPEARMINT OIL; GUAR HYDROXYPROPYLTRIMONIUM CHLORIDE (1.7 SUBSTITUENTS PER SACCHARIDE); ZINC SULFATE; DIMETHICONOL (41 MPA.S); DIMETHICONE; POLOXAMER 407; LAURETH-23; LAURETH-4; .ALPHA.-TOCOPHEROL ACETATE, D-; ALMOND OIL; POLYETHYLENE GLYCOL 400000; PANTHENOL; LYSINE HYDROCHLORIDE; HYDROGENATED COCONUT OIL; SOYBEAN OIL; ASIAN GINSENG; TEA TREE OIL; BUTYLENE GLYCOL; IODOPROPYNYL BUTYLCARBAMATE

Clear Men 2 in 1 Complete Care Anti Dandruff Shampoo and Conditioner

Active Ingredient

Pyrithione Zinc (1.0%)

Purpose

Anti-Dandruff

INDICATIONS AND USAGE

Use Helps prevent and control recurrence of itching and flaking associated with dandruff

Warnings
For external use only

When using this product Avoid contact with eyes. If contact occurs, rinse eyes thoroughly with water.

Stop use and ask a doctor if condition worsens or does not improve after regular use of this product as directed.

KEEP OUT OF REACH OF CHILDREN

Keep this and all drugs out of reach of children. If swallowed, get medical help or contact a Poison Control Center right away.

DOSAGE AND ADMINISTRATION

Directions Wet hair, massage into scalp, rinse. Repeat if desired. For best results use at least twice a week or as directed by a doctor.

Inactive Ingredients

Water (Aqua), Sodium Laureth Sulfate, Cocamidopropyl Betaine, Sodium Chloride, Fragrance (Parfum), Dimethiconol, Carbomer, Dimethicone, DMDM Hydantoin, Guar Hydroxypropyltrimonium Chloride, Citric Acid, Zinc Sulfate, TEA-Dodecylbenzenesulfonate, Poloxamer 407, Laureth-23, Butylene Glycol, Laureth-4, Lysine HCl, Tocopheryl Acetate, Panthenol, PPG-9, Iodopropynyl Butylcarbamate, PEG-4, Xanthan Gum, Helianthus Annuus (Sunflower) Seed Oil, Prunus Amygdalus Dulcis (Sweet Almond) Oil, Glycine Soja (Soybean) Oil, Cocos Nucifera (Coconut) Oil, Methylchloroisothiazolinone, Methylisothiazolinone, Melaleuca Alternifolia (Tea Tree) Leaf Extract, Panax Ginseng Root Extract, Mentha Viridis (Spearmint) Leaf Oil.

Questions, comments? 1-800-372-6389